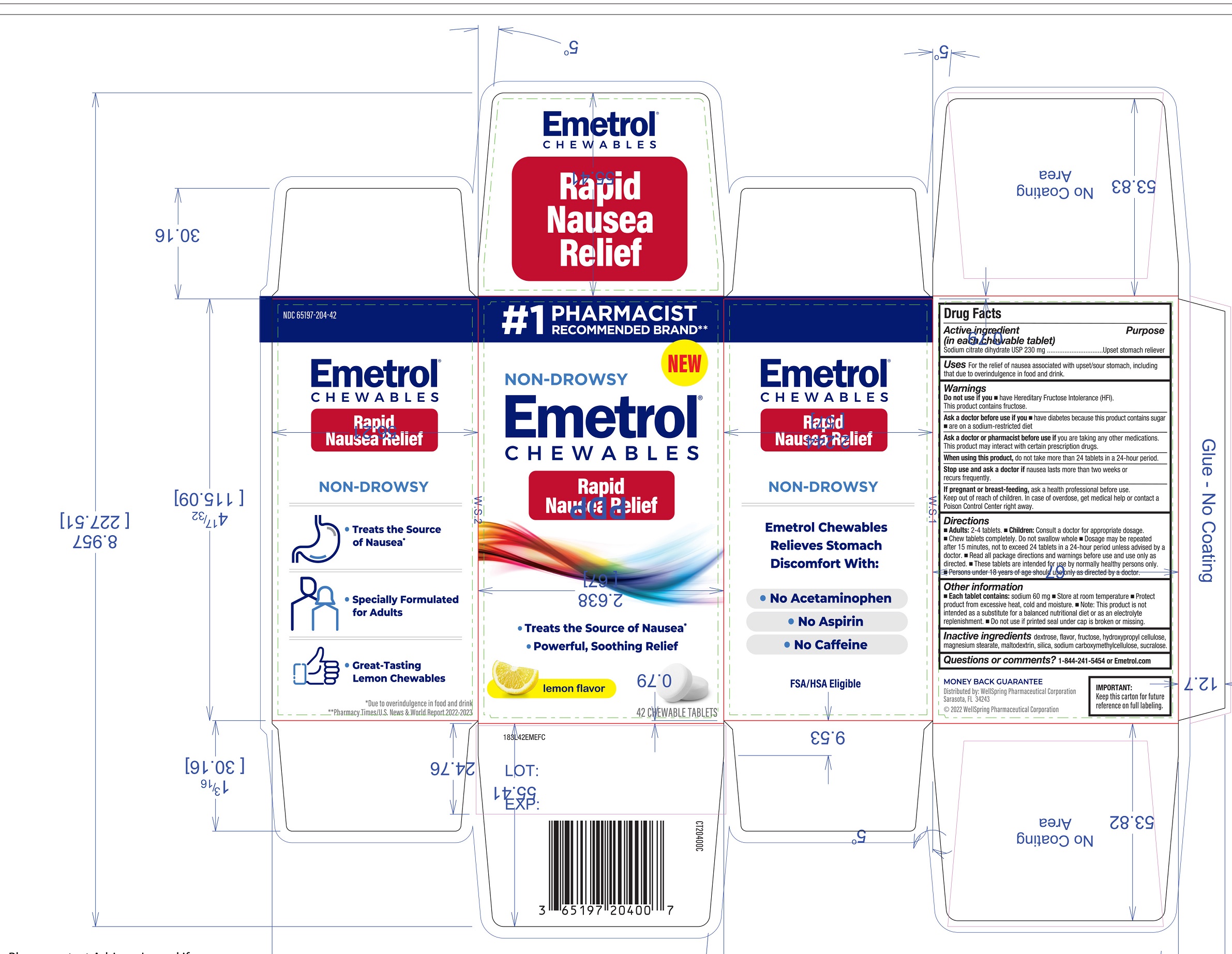 DRUG LABEL: Emetrol Chewables
NDC: 65197-204 | Form: TABLET, CHEWABLE
Manufacturer: WellSpring Pharmaceutical Corporation
Category: otc | Type: HUMAN OTC DRUG LABEL
Date: 20251120

ACTIVE INGREDIENTS: TRISODIUM CITRATE DIHYDRATE 230 mg/1 1
INACTIVE INGREDIENTS: DEXTROSE, UNSPECIFIED FORM; LEMON; FRUCTOSE; HYDROXYPROPYL CELLULOSE, UNSPECIFIED; MAGNESIUM STEARATE; MALTODEXTRIN; SILICON DIOXIDE; CARBOXYMETHYLCELLULOSE SODIUM, UNSPECIFIED; SUCRALOSE

Emetrol Chewables Rapid Nausea Relief

Active ingredients

- Sodium citrate dihydrate USP 230 mg

Purpose

Upset stomach reliever/antacid

Uses

For the relief of nausea associated with upset/sour stomach, including that due to overindulgence in food and drink.

Warnings

Do not use if you have

- Hereditary Fructose Intolerance (HFI). This product contains fructose.

Ask a doctor before use if you

- have diabetes because this product contains sugar
- are on a sodium-restricted diet

Ask a doctor or pharmacist before use if

- you are taking any other medications. This product may interact with certain prescription drugs.

When using this product,

- do not take more than 24 tablets in a 24-hour period.

Stop use and ask a doctor if

- nausea lasts more than two weeks or recurs frequently.

If pregnant or breast-feeding,

- ask a health professional before use. In case of overdose, get medical help or contact a Poison Control Center right away.

Directions

- Adults: 2-4 tablets.
- Children: Consult a doctor for appropriate dosage.
- Chew tablets completely. Do not swallow whole
- Dosage may be repeated after 15 minutes, not to exceed 24 tablets in a 24-hour period unless advised by a doctor.
- Read all package directions and warnings before use and use only as directed.
- These tablets are intended for use by normally healthy persons only.
- Persons under 18 years of age should use only as directed by a doctor.

Other information

- Each table contains: Sodium 60mg
- Store at room temperature
- Protect product from excessive heat, cold and moisture
- Note: This product is not intended as a substitute for a balanced nutritional diet or as an electrolyte replenishment.
- Do not use if printed seal under cap is broken or missing.

Inactive ingredients

dextrose, flavor, fructose, hydroxypropyl cellulose, magnesium stearate, maltodextrin, silica, sodium carboxymethylcellulose, sucralose.

Questions or Comments?

1-844-241-5454 or Emetrol.com

Distributed By

WellSpring Pharmaceutical Corporation
Sarasota, FL 34243
(c) 2022 WellSpring Pharmaceutical Corporation

PACKAGE LABEL

Pharmacy Recommended

New

Non-Drowsy

Emetrol Chewable Rapid Nausea Relief

Treats the source of Nausea*

*Due to overindulgence in food and drink

Powerful, Soothing Relief

Lemon Flavor

42 Chewable Tablets

Side Panels

Emetrol Chewables Rapid Nausea Relief

Non-Drowsy

Treats the source of Nausea*

Specially Formulated for Adults

Great-tasting Lemon Chewables

*Due to overindulgence in food and drink

Emetrol Chewables relieves stomach discomfort with:

No Acetaminophen

No Aspirin

No Caffeine